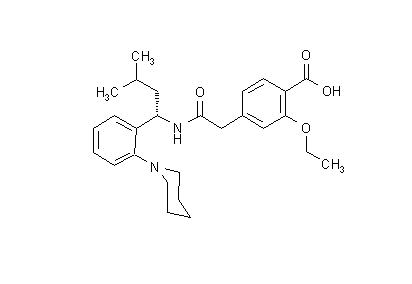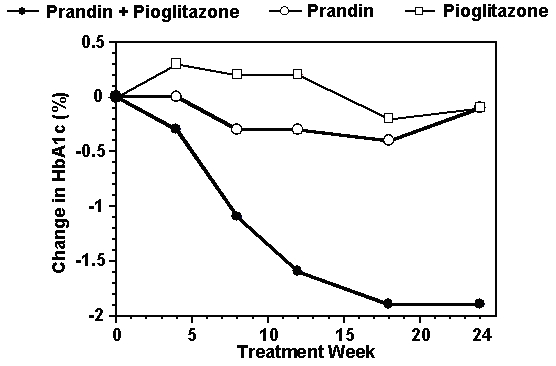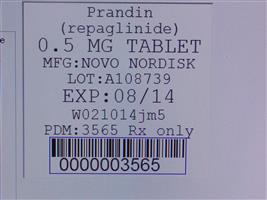 DRUG LABEL: Prandin
NDC: 68151-3565 | Form: TABLET
Manufacturer: Carilion Materials Management
Category: prescription | Type: HUMAN PRESCRIPTION DRUG LABEL
Date: 20171228

ACTIVE INGREDIENTS: REPAGLINIDE 0.5 mg/1 1

HIGHLIGHTS OF PRESCRIBING INFORMATION

These highlights do not include all the information needed to use PRANDIN safely and effectively. See full prescribing information for PRANDIN.
Initial U.S. Approval: 1997

RECENT MAJOR CHANGES

• Dosage and Administration (2.3) 2/2017

1 INDICATIONS AND USAGE

PRANDIN is a glinide indicated as an adjunct to diet and exercise to improve glycemic control in adults with type 2 diabetes mellitus (1)

Limitation of Use:

Not for treatment of type 1 diabetes mellitus or diabetic ketoacidosis (1)

2 DOSAGE AND ADMINISTRATION

- The recommended starting dose is 0.5 mg orally before each meal if HbA1c is less than 8%; and 1 or 2 mg orally before each meal if HbA1c is 8% or greater. (2.1)
- The recommended dose range is 0.5 mg to 4 mg before meals, with a maximum daily dose of 16 mg. (2.1)
- The patient’s dose should be doubled up to 4 mg with each meal until satisfactory glycemic control is achieved. At least one week should elapse to assess response after each dose adjustment. (2.1)
- Instruct patients to skip the dose of PRANDIN if a meal is skipped. In patients who experience hypoglycemia, the dose of PRANDIN should be reduced. (2.1; 5.1)
- Instruct patients to take PRANDIN within 30 minutes before meals. (2.1)
- In patients with severe renal impairment (CrCl = 20 – 40 mL/min), recommended starting dose is 0.5 mg orally before each meal. (2.2)
- Dose modifications are required when used concominantly with some medications. (2.3,7)

3 DOSAGE FORMS AND STRENGTHS

Tablets: 0.5 mg, 1 mg, 2 mg (3)

4 CONTRAINDICATIONS

- Concomitant use with gemfibrozil (4)
- Known hypersensitivity to repaglinide or any inactive ingredients (4)

5 WARNINGS AND PRECAUTIONS

• Hypoglycemia: PRANDIN may cause hypoglycemia. Skip the scheduled dose of PRANDIN if a meal is skipped to reduce the risk of hypoglycemia. Reduce the dose of PRANDIN if hypoglycemia occurs. (5.1)

• Serious Cardiovascular Adverse Reactions with Concomitant NPH-insulin: PRANDIN is not indicated for use in combination with NPH-insulin. (5.2)

• Macrovascular outcomes: There have been no clinical studies establishing conclusive evidence of macrovascular risk reduction with PRANDIN. (5.3)

6 ADVERSE REACTIONS

The most common adverse reactions (5% or greater incidence) among patients treated with PRANDIN were: hypoglycemia, upper respiratory infection, headache, sinusitis, arthralgia, nausea, diarrhea, and back pain. (6.1)

To report SUSPECTED ADVERSE REACTIONS, contact Novo Nordisk at 1-800-727-6500 or FDA at 1-800-FDA-1088 or www.fda.gov/medwatch.

7 DRUG INTERACTIONS

• Clopidogrel: Avoid concomitant use; if used concomitantly initiate at 0.5 mg before each meal and limit total daily dose to 4 mg (7)

• Cyclosporine: Limit daily dose of PRANDIN to 6 mg and increase frequency of glucose monitoring when co-administered (7)

• CYP2C8 and CYP3A4 Inhibitors and Drugs That May Increase the Risk of Hypoglycemia: Co-administration may require PRANDIN dose reductions and increased frequency of glucose monitoring (7)

• CYP2C8 and CYP3A4 Inducers and Drugs That May Decrease the Blood Glucose Lowering Effect of PRANDIN: Co-administration may require PRANDIN dose increases and increased frequency of glucose monitoring (7)

- Drugs That May Blunt Signs and Symptoms of Hypoglycemia: Increased frequency of glucose monitoring may be required when co-administered (7)

8 USE IN SPECIFIC POPULATIONS

- Nursing mothers: Discontinue PRANDIN or nursing (8.3)

FULL PRESCRIBING INFORMATION

1 INDICATIONS AND USAGE

PRANDIN is indicated as an adjunct to diet and exercise to improve glycemic control in adults with type 2 diabetes mellitus.

Limitation of Use:

PRANDIN should not be used in patients with type 1 diabetes mellitus or for the treatment of diabetic ketoacidosis.

2 DOSAGE AND ADMINISTRATION

2.1 Recommended Dosage and Administration

The recommended starting dose for patients whose HbA1c is less than 8% is 0.5 mg orally before each meal. For patients whose HbA1c is 8% or greater the starting dose is 1 or 2 mg orally before each meal.

The recommended dose range is 0.5 mg to 4 mg before meals, with a maximum daily dose of 16 mg. The patient’s dose should be doubled up to 4 mg with each meal until satisfactory glycemic control is achieved. At least one week should elapse to assess response after each dose adjustment.

Instruct patients to take PRANDIN within 30 minutes before meals. PRANDIN may be dosed 2, 3, or 4 times a day in response to changes in the patient’s meal pattern.

In patients who skip meals, instruct patients to skip the scheduled dose of PRANDIN to reduce the risk of hypoglycemia. In patients who experience hypoglycemia, the dose of PRANDIN should be reduced [see Warnings and Precautions (5.1)].

2.2 Patients with Severe Renal Impairment

In patients with severe renal impairment (CrCl = 20 – 40 mL/min) initiate PRANDIN 0.5 mg orally before each meal. Gradually titrate the dose, if needed to achieve glycemic control.

2.3 Dose Modifications for Drug Interactions

Dosage adjustments are recommended in patients taking concomitant strong CYP3A4 or CYP2C8 inhibitors or strong CYP3A4 or CYP2C8 inducers [see Drug Interactions (7), Clinical Pharmacology (12.3)].

Concomitant use with gemfibrozil is contraindicated [see Contraindications (4)].

Avoid concomitant use of PRANDIN with clopidogrel. If concomitant use can not be avoided, initiate PRANDIN at 0.5 mg before each meal and do not exceed a total daily dose of 4 mg [see Drug Interactions (7), Clinical Pharmacology (12.3)].

Do not exceed a total daily dose of 6 mg of PRANDIN in patients receiving cyclosporine [see Drug Interactions (7), Clinical Pharmacology (12.3)].

3 DOSAGE FORMS AND STRENGTHS

- 0.5 mg tablets (white, biconvex tablets, embossed with the Novo Nordisk (Apis) bull symbol)
- 1 mg tablets (yellow, biconvex tablets, embossed with the Novo Nordisk (Apis) bull symbol)
- 2 mg tablets (peach, biconvex tablets, embossed with the Novo Nordisk (Apis) bull symbol)

4 CONTRAINDICATIONS

PRANDIN is contraindicated in patients with:

- Concomitant use of gemfibrozil [see Drug Interactions (7)]
- Known hypersensitivity to repaglinide or any inactive ingredients

5 WARNINGS AND PRECAUTIONS

5.1 Hypoglycemia

All glinides, including PRANDIN, can cause hypoglycemia [see Adverse Reactions (6.1)]. Severe hypoglycemia can cause seizures, may be life-threatening, or cause death. Hypoglycemia can impair concentration ability and reaction time; this may place an individual and others at risk in situations where these abilities are important (e.g., driving or operating other machinery).

Hypoglycemia can happen suddenly and symptoms may differ in each individual and change over time in the same individual. Symptomatic awareness of hypoglycemia may be less pronounced in patients with longstanding diabetes, in patients with diabetic nerve disease, in patients using medications that block the sympathetic nervous system (e.g., beta-blockers) [see Drug Interactions (7)], or in patients who experience recurrent hypoglycemia.

Factors which may increase the risk of hypoglycemia include changes in meal pattern (e.g., macronutrient content), changes in level of physical activity, changes to co-administered medication [see Drug Interactions (7)], and concomitant use with other antidiabetic agents. Patients with renal or hepatic impairment may be at higher risk of hypoglycemia [see Use in Specific Populations (8.6, 8.7)].

Patients should administer PRANDIN before meals and be instructed to skip the dose of PRANDIN if a meal is skipped. In patients who experience hypoglycemia, the dose of PRANDIN should be reduced [see Dosage and Administration (2.1)]. Patients and caregivers must be educated to recognize and manage hypoglycemia. Self-monitoring of blood glucose plays an essential role in the prevention and management of hypoglycemia. In patients at higher risk for hypoglycemia and patients who have reduced symptomatic awareness of hypoglycemia, increased frequency of blood glucose monitoring is recommended.

5.2 Serious Cardiovascular Adverse Reactions with Concomitant Use with NPH-insulin

Across seven controlled trials, there were six serious adverse events of myocardial ischemia in patients treated with PRANDIN plus NPH-insulin from two studies, and one event in patients using insulin formulations alone from another study [See Adverse Reactions (6.1)]. PRANDIN is not indicated for use in combination with NPH-insulin.

5.3 Macrovascular Outcomes

There have been no clinical studies establishing conclusive evidence of macrovascular risk reduction with PRANDIN.

6 ADVERSE REACTIONS

The following serious adverse reaction is also described elsewhere in the labeling:

Hypoglycemia [see Warnings and Precautions (5.1)]

6.1 Clinical Trials Experience

Because clinical trials are conducted under widely varying designs, the adverse reaction rates reported in one clinical trial may not be easily compared to those rates reported in another clinical trial, and may not reflect the rates actually observed in clinical practice.

PRANDIN has been administered to 2931 individuals during clinical trials. Approximately 1500 of these individuals with type 2 diabetes have been treated for at least 3 months, 1000 for at least 6 months, and 800 for at least 1 year. The majority of these individuals (1228) received PRANDIN in one of five 1-year, active-controlled trials. Over one year, 13% of PRANDIN patients were discontinued due to adverse reactions. The most common adverse reactions leading to withdrawal were hyperglycemia, hypoglycemia, and related symptoms.

Table 1 lists the common adverse reactions for PRANDIN patients compared to placebo in trials 12 to 24 weeks duration.

Table 1: Adverse Reactions (%) occurring ≥ 2% in PRANDIN Treated Patients from Pool of 12 to 24 Week Placebo Controlled Trials*

 | PRANDIN; N=352 | Placebo; N=108
Upper Respiratory Infection | 16 | 8
Headache | 11 | 10
Sinusitis | 6 | 2
Arthralgia | 6 | 3
Nausea | 5 | 5
Diarrhea | 5 | 2
Back Pain | 5 | 4
Rhinitis | 3 | 3
Constipation | 3 | 2
Vomiting | 3 | 3
Paresthesia | 3 | 3
Chest pain | 3 | 1
Bronchitis | 2 | 1
Dyspepsia | 2 | 2
Urinary tract infection | 2 | 1
Tooth disorder | 2 | 0
Allergy | 2 | 0

*See trial descriptions in Clinical Trials (14)

Hypoglycemia

In clinical trials with PRANDIN, hypoglycemia is the most commonly observed adverse reaction. Mild or moderate hypoglycemia occurred in 31% of PRANDIN treated patients and 7% of placebo treated patients [see Warnings and Precautions (5.1]).

Hypoglycemia was reported in 16% of 1228 PRANDIN patients, 20% of 417 glyburide patients, and 19% of 81 glipizide patients in 1-year controlled trials. Of PRANDIN-treated patients with symptomatic hypoglycemia, none developed coma or required hospitalization.

In a 24-week placebo controlled trial, patients who were naïve to oral hypoglycemic agent therapy and patients with a HbA1c below 8% at baseline had a higher frequency of hypoglycemia.

Weight Gain

There was no average gain in body weight when patients previously treated with oral hypoglycemic agents were switched to PRANDIN. The average weight gain in patients treated with PRANDIN and not previously treated with sulfonylurea drugs was 3.3%.

Cardiovascular Events

The incidence of total serious cardiovascular adverse events, including ischemia, was higher for PRANDIN (51/1228 or 4%) than for sulfonylurea drugs (13/498 or 3%) in controlled comparator clinical trials.

Table 2: Summary of Serious Cardiovascular Events in Trials Comparing PRANDIN to Sulfonylureas (% of total patients with events)

 | PRANDIN | SU*
Total Exposed | 1228 | 498
Serious CV Events | 4% | 3%
Cardiac Ischemic Events | 2% | 2%
Deaths due to CV Events | 0.5% | 0.4%

*: glyburide and glipizide

Seven controlled clinical trials included PRANDIN combination therapy with NPH-insulin (n=431), insulin formulations alone (n=388) or other combinations (sulfonylurea plus NPH-insulin or PRANDIN plus metformin) (n=120). There were six serious adverse events of myocardial ischemia in patients treated with PRANDIN plus NPH-insulin from two studies, and one event in patients using insulin formulations alone from another study [see Warnings and Precautions (5.3)].

Combination Therapy with Thiazolidinediones
Hypoglycemia

During 24-week treatment clinical trials of PRANDIN-rosiglitazone or PRANDIN-pioglitazone combination therapy (a total of 250 patients in combination therapy), hypoglycemia (blood glucose < 50 mg/dL) occurred in 7% of patients in combination therapy compared to 7% for PRANDIN monotherapy, and 2% for thiazolidinedione monotherapy.

Peripheral Edema and Heart Failure

Peripheral edema was reported in 12 out of 250 (4.8%) PRANDIN-thiazolidinedione combination therapy patients and 3 out of 124 (2.4%) thiazolidinedione monotherapy patients, with no cases reported in these trials for PRANDIN monotherapy. There were reports in 2 of 250 patients (0.8%) treated with PRANDIN-thiazolidinedione therapy of episodes of edema with congestive heart failure. Both patients had a prior history of coronary artery disease and recovered after treatment with diuretic agents. No comparable cases in the monotherapy treatment groups were reported.

Weight Gain

Mean weight increases associated with combination, PRANDIN and pioglitazone therapy were 5.5 kg, 0.3 kg, and 2.0 kg respectively. Mean weight increases associated with combination, PRANDIN and rosiglitazone therapy were 4.5 kg, 1.3 kg, and 3.3 kg respectively.

Infrequent Adverse Events (<1% of Patients)

Less common adverse clinical or laboratory events observed in clinical trials included elevated liver enzymes, thrombocytopenia, leukopenia, and anaphylactoid reactions.

6.2 Postmarketing Experience

The following additional adverse reactions have been identified during post approval use of PRANDIN. Because these reactions are reported voluntarily from a population of uncertain size, it is generally not possible to reliably estimate their frequency or a causal relationship to drug exposure.

- Alopecia
- Hemolytic anemia
- Pancreatitis
- Stevens-Johnson Syndrome
- Severe hepatic dysfunction including jaundice and hepatitis

7 DRUG INTERACTIONS

Clinically Important Drug Interactions with PRANDIN

Table 3 includes a list of drugs with clinically important drug interactions when administered concomitantly with PRANDIN and instructions for preventing or managing them.

Table 3: Clinically Important Drug Interactions with PRANDIN

Gemfibrozil
Clinical Impact: | Gemfibrozil significantly increased repaglinide exposures by 8.1 fold [see Clinical Pharmacology (12.3)]
Intervention: | Do not administer PRANDIN to patients receiving gemfibrozil [see Contraindications (4)].
Clopidogrel
Clinical Impact: | Clopidogrel increased repaglinide exposures by 3.9-5.1 fold [see Clinical Pharmacology (12.3)]
Intervention: | Avoid concomitant use of PRANDIN with clopidogrel. If concomitant use can not be avoided, initiate PRANDIN at 0.5 mg before each meal and do not exceed a total daily dose of 4 mg [see DOSAGE AND ADMINISTRATION (2.3)]. Increased frequency of glucose monitoring may be required during concomitant use.
Cyclosporine
Clinical Impact: | Cyclosporine increased low dose repaglinide exposures by 2.5 fold [see Clinical Pharmacology (12.3)]
Intervention: | Daily maximum PRANDIN dose should be limited to 6 mg, and increased frequency of glucose monitoring may be required when PRANDIN is co-administered with cyclosporine.
CYP2C8 and CYP3A4 Inhibitors
Intervention: | PRANDIN dose reductions and increased frequency of glucose monitoring may be required when co-administered.
Examples: | Drugs that are known to inhibit CYP3A4 include antifungal agents (ketoconazole, itraconazole) and antibacterial agents (clarithromycin, erythromycin). Drugs that are known to inhibit CYP2C8 include trimethoprim, gemfibrozil, montelukast, deferasirox, and clopidiogrel.
CYP2C8 and CYP3A4 Inducers
Intervention: | PRANDIN dose increases and increased frequency of glucose monitoring may be required when co-administered.
Examples: | Drugs that induce the CYP3A4 and/or 2C8 enzyme systems include rifampin, barbiturates, and carbamezapine
Drugs That May Increase the Risk of Hypoglycemia
Intervention: | PRANDIN dose reductions and increased frequency of glucose monitoring may be required when co-administered.
Examples: | Antidiabetic agents, ACE inhibitors, angiotensin II receptor blocking agents, disopyramide, fibrates, fluoxetine, monoamine oxidase inhibitors, nonsteroidal anti-inflammatory agents (NSAIDs), pentoxifylline, pramlintide, propoxyphene, salicylates, somatostatin analogs (e.g., octreotide), and sulfonamide antibiotics
Drugs That May Decrease the Blood Glucose Lowering Effect of PRANDIN
Intervention: | PRANDIN dose increases and increased frequency of glucose monitoring may be required when co-administered.
Examples: | Atypical antipsychotics (e.g., olanzapine and clozapine), calcium channel antagonists, corticosteroids, danazol, diuretics, estrogens, glucagon, isoniazid, niacin, oral contraceptives, phenothiazines, progestogens (e.g., in oral contraceptives), protease inhibitors, somatropin, sympathomimetic agents (e.g., albuterol, epinephrine, terbutaline), and thyroid hormones.
Drugs That May Blunt Signs and Symptoms of Hypoglycemia
Intervention: | Increased frequency of glucose monitoring may be required when PRANDIN is co-administered with these drugs.
Examples: | beta-blockers, clonidine, guanethidine, and reserpine

8 USE IN SPECIFIC POPULATIONS

8.1 Pregnancy

Pregnancy Category C.

There are no adequate and well-controlled studies in pregnant women. It is unknown whether PRANDIN can cause fetal harm when administered to a pregnant woman. PRANDIN should be used during pregnancy only if the potential benefit justifies the potential risk to the fetus.

Repaglinide was not teratogenic in rats or rabbits at doses 40 times (rats) and approximately 0.8 times (rabbit) clinical exposure (on a mg/m^2 basis) throughout pregnancy. Offspring of rat dams exposed to repaglinide at 15 times clinical exposure on a mg/m^2 basis during days 17 to 22 of gestation and during lactation developed nonteratogenic skeletal deformities consisting of shortening, thickening, and bending of the humerus during the postnatal period. This effect was not seen at doses up to 2.5 times clinical exposure (on a mg/m^2 basis) on days 1 to 22 of pregnancy or at higher doses given during days 1 to 16 of pregnancy. Relevant human exposure has not occurred to date and therefore the safety of PRANDIN administration throughout pregnancy or lactation cannot be established.

8.3 Nursing Mothers

Although it is not known whether repaglinide is excreted in human milk some oral agents are known to be excreted by this route. Because the potential for hypoglycemia in nursing infants may exist, and because of the effects on nursing animals, a decision should be made as to whether PRANDIN should be discontinued in nursing mothers, or if mothers should discontinue nursing. If PRANDIN is discontinued and if diet alone is inadequate for controlling blood glucose, insulin therapy should be considered. In rat reproduction studies, measurable levels of repaglinide were detected in the breast milk of the dams and lowered blood glucose levels were observed in the pups. Cross fostering studies indicated that skeletal changes [see Use in Specific Populations (8.1)] could be induced in control pups nursed by treated dams, although this occurred to a lesser degree than those pups treated in utero.

8.4 Pediatric Use

Safety and effectiveness have not been established in pediatric patients.

8.5 Geriatric Use

In clinical studies of 24 weeks or greater duration, 415 patients were over 65 years of age and no patients were greater than 75 years of age. In one-year, active-controlled trials, no differences were seen in effectiveness or adverse events between these subjects and those less than 65. There was no increase in frequency or severity of hypoglycemia in older subjects, but greater sensitivity of some older individuals to PRANDIN therapy cannot be ruled out.

8.6 Renal Impairment

Pharmacokinetic studies of repaglinide were conducted in patients with mild to moderate renal function impairment (CrCl = 40 – 80 mL/min), and severe renal function impairment (CrCl = 20 – 40 mL/min). Initial dose adjustment is not required in patients with mild to moderate renal dysfunction. However, patients with severe renal function impairment should initiate PRANDIN therapy with the 0.5 mg dose and be carefully titrated [see Dosage and Administration (2.2)].

Studies were not conducted in patients with creatinine clearances below 20 mL/min or patients with renal failure requiring hemodialysis.

8.7 Hepatic Impairment

A single-dose study was conducted 12 patients with chronic liver disease. Patients with moderate to severe impairment of liver function had higher and more prolonged serum concentrations. Therefore, PRANDIN should be used cautiously in patients with impaired liver function. Longer intervals between dose adjustments may be needed to allow full assessment of response.

10 OVERDOSAGE

Severe hypoglycemic reactions with coma, seizure, or other neurological impairment may occur and constitute medical emergencies requiring immediate hospitalization. Hypoglycemic symptoms without loss of consciousness or neurologic findings should be treated aggressively with oral glucose and adjustments in drug dosage and/or meal patterns. Close monitoring may continue until the physician is assured that the patient is out of danger. Patients should be closely monitored for a minimum of 24 to 48 hours, since hypoglycemia may recur after apparent clinical recovery. There is no evidence that PRANDIN is dialyzable using hemodialysis.

11 DESCRIPTION

PRANDIN (repaglinide) is an oral blood glucose-lowering drug of the glinide class. Repaglinide, S(+)2-ethoxy-4(2((3-methyl-1-(2-(1-piperidinyl) phenyl)-butyl) amino)-2-oxoethyl) benzoic acid, is chemically unrelated to the oral sulfonylurea insulin secretagogues.

Structural Formula of Repaglinide

Repaglinide is a white to off-white powder with molecular formula C27 H36 N2 O4 and a molecular weight of 452.6. PRANDIN tablets contain 0.5 mg, 1 mg, or 2 mg of repaglinide. In addition each tablet contains the following inactive ingredients: calcium hydrogen phosphate (anhydrous), microcrystalline cellulose, maize starch, polacrilin potassium, povidone, glycerol (85%), magnesium stearate, meglumine, and poloxamer. The 1 mg and 2 mg tablets contain iron oxides (yellow and red, respectively) as coloring agents.

12 CLINICAL PHARMACOLOGY

12.1 Mechanism of Action

Repaglinide lowers blood glucose levels by stimulating the release of insulin from the pancreas. This action is dependent upon functioning beta (ß) cells in the pancreatic islets. Insulin release is glucose-dependent and diminishes at low glucose concentrations.

Repaglinide closes ATP-dependent potassium channels in the ß-cell membrane by binding at characterizable sites. This potassium channel blockade depolarizes the ß-cell, which leads to an opening of calcium channels. The resulting increased calcium influx induces insulin secretion. The ion channel mechanism is highly tissue selective with low affinity for heart and skeletal muscle.

12.2 Pharmacodynamics

A four-week, double-blind, placebo-controlled dose-response trial was conducted in 138 patients with type 2 diabetes using doses ranging from 0.25 (not an approved dose) to 4 mg taken with each of three meals. PRANDIN therapy resulted in dose-proportional glucose lowering over the full dose range. Plasma insulin levels increased after meals and reverted toward baseline before the next meal. Most of the fasting blood glucose-lowering effect was demonstrated within 1-2 weeks.

In a double-blind, placebo-controlled, 3-month dose titration study, PRANDIN or placebo doses for each patient were increased weekly from 0.25 mg (not an approved dose) through 0.5, 1, and 2 mg, to a maximum of 4 mg, until a fasting plasma glucose (FPG) level <160 mg/dL was achieved or the maximum dose reached. The dose that achieved the targeted control or the maximum dose was continued to end of study. FPG and 2-hour post-prandial glucose (PPG) increased in patients receiving placebo and decreased in patients treated with repaglinide. Differences between the repaglinide- and placebo-treated groups were -61 mg/dL (FPG) and ‑104 mg/dL (PPG) (Table 4).

Table 4: PRANDIN vs Placebo:

Mean Change from Baseline after 3 Months of Treatment

 | Repaglinide | Placebo
N | 66 | 33
Fasting Plasma Glucose (mg/dL)
Baseline | 220.2 | 215.3
Change from baseline; (at last visit) | -31.0* | 30.3
Post Prandial Glucose (mg/dL)
Baseline | 261.7 | 245.2
Change from baseline; (at last visit) | -47.6* | 56.5

*: p< 0.05 for between group difference

The dosing of PRANDIN relative to meal-related insulin release was studied in three trials including 58 patients. Glycemic control was maintained during a period in which the meal and dosing pattern was varied (2, 3 or 4 meals per day; before meals x 2, 3, or 4) compared with a period of 3 regular meals and 3 doses per day (before meals x 3). Blood glucose-lowering effect did not differ when PRANDIN was administered at the start of a meal, 15 minutes before, or 30 minutes before the meal.

12.3 Pharmacokinetics

The pharmacokinetic parameters of repaglinide obtained from a single-dose, crossover study in healthy subjects and from a multiple‑dose, parallel, dose-proportionality (0.5, 1, 2 and 4 mg) study in patients with type 2 diabetes are summarized in Tables 5 and 6. These data indicate that repaglinide did not accumulate in serum. Clearance of oral repaglinide did not change over the 0.5 - 4 mg dose range, indicating a linear relationship between dose and plasma drug levels.

Table 5: Pharmacokinetic Parameters for Repaglinide in Healthy Subjects

Parameter
CL (based on i.v.) | 38 ± 16 L/hr
Vss (based on i.v.) | 31 ± 12 L
AbsBio | 56 ± 9%

CL = total body clearance
V ss = volume of distribution at steady state
AbsBio = absolute bioavailability

Table 6: Pharmacokinetic Parameters for Repaglinide in Patients with Type 2 Diabetes*

 | Pharmacokinetic Parameter
Dose; (mg) | AUC0-24 hr (ng/mL*hr); Mean (SD) | Cmax0-5 hr (ng/mL); Mean (SD)
0.5 | 68.9 (154.4) | 9.8 (10.2)
1 | 125.8 (129.8) | 18.3 (9.1)
2 | 152.4 (89.60) | 26.0 (13.0)
4 | 447.4 (211.3) | 65.8 (30.1)
 | Tmax0-5 hr; Means (SD) | T½; Means (Ind Range)
0.5 - 4 | 1.0 – 1.4 (0.3 – 0.5) hr | 1.0 – 1.4 (0.4 – 8.0) hr

*dosed preprandially with three meals

Absorption

After oral administration, repaglinide is completely absorbed from the gastrointestinal tract. After single and multiple oral doses in healthy subjects or in patients, peak plasma drug levels (Cmax) occur within 1 hour (Tmax). Repaglinide is eliminated from the blood stream with a half-life of approximately 1 hour. The mean absolute bioavailability is 56%. When repaglinide was given with food, the mean Tmax was not changed, but the mean Cmax and AUC (area under the time/plasma concentration curve) were decreased 20% and 12.4%, respectively.

Distribution

After intravenous (IV) dosing in healthy subjects, the volume of distribution at steady state (Vss) was 31 L, and the total body clearance (CL) was 38 L/h. Protein binding and binding to human serum albumin was greater than 98%.

Metabolism and Elimination

Repaglinide is completely metabolized by oxidative biotransformation and direct conjugation with glucuronic acid after either an IV or oral dose. The major metabolites are an oxidized dicarboxylic acid (M2), the aromatic amine (M1), and the acyl glucuronide (M7). The cytochrome P-450 enzyme system, specifically 2C8 and 3A4, have been shown to be involved in the N‑dealkylation of repaglinide to M2 and the further oxidation to M1. Metabolites do not contribute to the glucose‑lowering effect of repaglinide.

Within 96 hours after dosing with ^14C-repaglinide as a single, oral dose, approximately 90% of the radiolabel was recovered in the feces and approximately 8% in the urine. Only 0.1% of the dose is cleared in the urine as parent compound. The major metabolite (M2) accounted for 60% of the administered dose. Less than 2% of parent drug was recovered in feces. Repaglinide appears to be a substrate for active hepatic uptake transporter (organic anion transporting protein OATP1B1).

Variability of Exposure

Repaglinide AUC after multiple doses of 0.25 to 4 mg with each meal varies over a wide range. The intra-individual and inter-individual coefficients of variation were 36% and 69%, respectively. AUC over the therapeutic dose range included 69 to 1005 ng/mL*hr, but AUC exposure up to 5417 ng/mL*hr was reached in dose escalation studies without apparent adverse consequences.

Specific Populations

Geriatric

Healthy volunteers were treated with a regimen of 2 mg PRANDIN taken before each of 3 meals. There were no significant differences in repaglinide pharmacokinetics between the group of patients <65 years of age and a comparably sized group of patients ≥65 years of age [see Use in Specific Populations (8.5)].

Gender

A comparison of pharmacokinetics in males and females showed the AUC over the 0.5 mg to 4 mg dose range to be 15% to 70% higher in females with type 2 diabetes. This difference was not reflected in the frequency of hypoglycemic episodes (male: 16%; female: 17%) or other adverse events.

Race

No pharmacokinetic studies to assess the effects of race have been performed, but in a U.S. 1-year study in patients with type 2 diabetes, the blood glucose-lowering effect was comparable between Caucasians (n=297) and African-Americans (n=33). In a U.S. dose-response study, there was no apparent difference in exposure (AUC) between Caucasians (n=74) and Hispanics (n=33).

Renal Impairment

Single-dose and steady-state pharmacokinetics of repaglinide were compared between patients with type 2 diabetes and normal renal function (CrCl > 80 mL/min), mild to moderate renal function impairment (CrCl = 40 – 80 mL/min), and severe renal function impairment (CrCl = 20 – 40 mL/min). Both AUC and Cmax of repaglinide were similar in patients with normal and mild to moderately impaired renal function (mean values 56.7 ng/mL*hr vs 57.2 ng/mL*hr and 37.5 ng/mL vs 37.7 ng/mL, respectively.) Patients with severely reduced renal function had elevated mean AUC and Cmax values (98.0 ng/mL*hr and 50.7 ng/mL, respectively), but this study showed only a weak correlation between repaglinide levels and creatinine clearance.

Hepatic Impairment

A single-dose, open-label study was conducted in 12 healthy subjects and 12 patients with chronic liver disease (CLD) classified by Child-Pugh scale and caffeine clearance. Patients with moderate to severe impairment of liver function had higher and more prolonged serum concentrations of both total and unbound repaglinide than healthy subjects (AUChealthy: 91.6 ng/mL*hr; AUCCLD patients: 368.9 ng/mL*hr; Cmax, healthy: 46.7 ng/mL; Cmax, CLD patients: 105.4 ng/mL). AUC was statistically correlated with caffeine clearance. No difference in glucose profiles was observed across patient groups.

Drug-Drug Interactions

Drug interaction studies performed in healthy volunteers show that PRANDIN had no clinically relevant effect on the pharmacokinetic properties of digoxin, theophylline, or warfarin. Co-administration of cimetidine with PRANDIN did not significantly alter the absorption and disposition of repaglinide.

Additionally, the following drugs were studied in healthy volunteers with co-administration of PRANDIN.

Table 7: Effect of Other Drugs on AUC and Cmax of Repaglinide
Study Drug | Dosing | Repaglinide Dosing^1 | Repaglinide
Study Drug | Dosing | Repaglinide Dosing^1 | AUC | Cmax
Clarithromycin* | 250 mg BID; for 4 days |  | 40% ↑ | 67% ↑
Clopidogrel* | 300 mg (Day 1); 75 mg QD (Day 2-3) | 0.25 mg; (Day 1 and 3) | (day 1) 5.1 fold ↑; (3.9-6.6); (day 3) 3.9 fold ↑; (2.9-5.3) | 2.5 fold ↑; (1.8-3.5); 2.0 fold ↑; (1.3-3.1)
Cyclosporine | 100 mg; (2 doses 12 hours apart) |  | 2.5 fold ↑ | 1.8 fold ↑
Deferasirox* | 30 mg/kg QD; for 4 days | 0.5 mg | 2.3 fold ↑ | 62% ↑
Fenofibrate | 200 mg QD; for 5 days |  | 0% | 0%
Gemfibrozil* | 600 mg BID; for 3 days |  | 8.1 fold ↑ | 2.4 fold ↑
Itraconazole* | 100 mg BID; for 3 days |  | 1.4 fold ↑ | 1.5 fold ↑
Gemfibrozil + Itraconazole* Co-administration | Gem: 600 mg BID; for 3 days; Itra: 100 mg BID; for 3 days |  | 19 fold ↑ | 2.8 fold ↑
Ketoconazole | 200 mg QD; for 4 days | 2 mg | 15% ↑ | 16% ↑
Levonorgestrel/ethinyl Estradiol | (0.15 mg/0.03 mg) Combination tablet QD; for 21 days | 2 mg | 0% | 20% ↑
Nifedipine* | 10 mg TID; for 4 days | 2 mg | 0% | 0%
Rifampin* | 600 mg QD; for 6-7 days | 4 mg | 32 – 80% ↓ | 17 - 79% ↓
Simvastatin | 20 mg QD; for 4 days | 2 mg | 0% | 26% ↑
Trimethoprim* | 160 mg BID; for 2 days; 160 mg QD; for 1 day |  | 61% ↑ | 41% ↑

^1 Unless indicated all drug interactions were observed with single dose of 0.25 mg repaglinide

↑ indicates increase

↓ indicates decrease

* Indicates data are from published literature

13 NONCLINICAL TOXICOLOGY

13.1 Carcinogenesis, Mutagenesis, Impairment of Fertility

In a 104-week carcinogenicity study in rats at doses up to 120 mg/kg/day, which is approximately 60 times clinical exposure on a mg/m2 basis, the incidences of benign adenomas of the thyroid and liver were increased in male rats. No evidence of carcinogenicity was found in female rats. The higher incidences of thyroid and liver tumors in male rats were not seen at lower dose of 30 mg/kg/day and 60 mg/kg/day respectively (which are over 15 and 30 times, respectively, clinical exposures on a mg/m^2 basis). In a 104-week carcinogenicity study in mice at doses up to 500 mg/kg/day, no evidence of carcinogenicity was found in mice (which is approximately 125 times clinical exposure on a mg/m^2 basis).

Repaglinide was non-genotoxic in a battery of in vivo and in vitro studies: Bacterial mutagenesis (Ames test), in vitro forward cell mutation assay in V79 cells (HGPRT), in vitro chromosomal aberration assay in human lymphocytes, unscheduled and replicating DNA synthesis in rat liver, and in vivo mouse and rat micronucleus tests.

In a rat fertility study, repaglinide was administered to male and female rats at doses up to 300 and 80 mg/kg/day, respectively. No adverse effects on fertility were observed (which are over 40 times clinical exposure on a mg/m^2 basis).

14 CLINICAL STUDIES

14.1 Monotherapy Trials

A double-blind, placebo-controlled trial was carried out in 362 patients treated for 24 weeks. HbA1c for the PRANDIN-treated groups (1 and 4 mg groups combined) at the end of the study was decreased compared to the placebo-treated group in treatment naïve patients and in patients previously treated with oral hypoglycemic agents by 2.1% and 1.7%, respectively. In this fixed-dose trial, patients who were treatment naïve to oral hypoglycemic agent therapy and patients with a HbA1c below 8% at baseline showed greater blood glucose-lowering.

14.2 Combination Trials

PRANDIN in Combination With Metformin

PRANDIN was studied in combination with metformin in 83 patients not satisfactorily controlled on exercise, diet, and metformin alone. PRANDIN dosage was titrated for 4 to 8 weeks, followed by a 3-month maintenance period. Combination therapy with PRANDIN and metformin resulted in statistically significant improvement in HbA1c and fasting plasma glucose (FPG) compared to PRANDIN or metformin monotherapy (Table 8). In this study where metformin dosage was kept constant, the combination therapy of PRANDIN and metformin showed dose-sparing effects with respect to PRANDIN. The improvement in HbA1c and FPG of the combination group was achieved at a lower daily PRANDIN dosage than in the PRANDIN monotherapy group (Table 8).

Table 8: PRANDIN in Combination with Metformin:

Mean Change from Baseline after 4 to 5 Months of Treatment^1

 | PRANDIN; Monotherapy | PRANDIN; Combination Therapy; with Metformin | Metformin; Monotherapy
N | 28 | 27 | 27
Median Final Dose (mg/day) | 12 | 6 (PRANDIN); 1500 (metformin) | 1500
HbA1c (%)
Baseline | 8.6 | 8.3 | 8.6
Change from baseline | -0.38 | -1.41* | -0.33
Fasting Plasma Glucose (mg/dL)
Baseline | 174 | 184 | 194
Change from baseline | 8.8 | -39.2* | -4.5
Weight (kg)
Baseline | 87 | 93 | 91
Change from baseline | 3.0 | 2.4# | -0.90

^1: based on intent-to-treat analysis

*: p< 0.05, for pairwise comparisons with PRANDIN and metformin monotherapy.

#: p< 0.05, for pairwise comparison with metformin.

PRANDIN in Combination With Pioglitazone

A combination therapy regimen of PRANDIN and pioglitazone (N=123) was compared to PRANDIN alone (N=61) and pioglitazone alone (N=62) in a 24-week trial that enrolled 246 patients previously treated with sulfonylurea or metformin monotherapy (HbA1c > 7.0%). PRANDIN dosage was titrated during the first 12 weeks, followed by a 12-week maintenance period. Combination therapy resulted in statistically significant improvement in HbA1c and FPG compared to monotherapy (Figure 1). The changes from baseline for completers in FPG (mg/dL) and HbA1c (%), respectively were: -39.8 mg/dL and -0.1% for PRANDIN, -35.3 mg/dL and -0.1% for pioglitazone and -92.4 mg/dL and -1.9% for the combination. In this study where pioglitazone dosage was kept constant, the combination therapy group showed dose-sparing effects with respect to PRANDIN (see Figure 1 Legend). The improvement in HbA1c and FPG of the combination group was achieved at a lower daily PRANDIN dosage than in the PRANDIN monotherapy group.

Figure 1: PRANDIN in Combination with Pioglitazone: HbA1c Values

LEGEND: HbA1c values by study week for patients who completed study (combination, N = 101; PRANDIN, N = 35, pioglitazone, N = 26).

Subjects with FPG above 270 mg/dL were withdrawn from the study.

Pioglitazone dose: fixed at 30 mg/day; PRANDIN median final dose: 6 mg/day for combination and 10 mg/day for monotherapy.

PRANDIN in Combination With Rosiglitazone

A combination therapy regimen of PRANDIN and rosiglitazone was compared to monotherapy with either agent alone in a 24-week trial that enrolled 252 patients previously treated with sulfonylurea or metformin (HbA1c > 7.0%). Combination therapy resulted in statistically significant improvement in HbA1c and FPG compared to monotherapy (Table 9 below). The glycemic effects of the combination therapy were dose-sparing with respect to both total daily PRANDIN dosage and total daily rosiglitazone dosage (see Table 9 Legend). The improvement in HbA1c and FPG of the combination therapy group was achieved with lower daily dose of PRANDIN and rosiglitazone, as compared to the respective monotherapy groups.

Table 9: PRANDIN in Combination with Rosiglitazone:

Mean Change from Baseline in a 24-Week Study^1

 | PRANDIN; Monotherapy | PRANDIN; Combination Therapy; with Rosiglitazone | Rosiglitazone; Monotherapy
N | 63 | 127 | 62
Median Final Dose (mg/day) | 12 | 6 (PRANDIN); 4 (Rosiglitazone) | 8
HbA1c (%)
Baseline | 9.3 | 9.1 | 9.0
Change from baseline | -0.17 | -1.43 | -0.56
Fasting Plasma Glucose (mg/dL)
Baseline | 269 | 257 | 252
Change from baseline | -54 | -94* | -67
Change in Weight (kg) | +1.3 | +4.5# | +3.3

^1: based on intent-to-treat analysis

*: p-value ≤ 0.001 for comparison to either monotherapy

#: p-value < 0.001 for comparison to PRANDIN

16 HOW SUPPLIED/STORAGE AND HANDLING

Product: 68151-3565

NDC: 68151-3565-8 1 TABLET in a PACKAGE

17 PATIENT COUNSELING INFORMATION

Hypoglycemia

Inform patients that PRANDIN can cause hypoglycemia and instruct patients and their caregivers on self-management procedures including glucose monitoring and management of hypoglycemia. Inform patients that their ability to concentrate and react may be impaired as a result of hypoglycemia. In patients at higher risk for hypoglycemia and patients who have reduced symptomatic awareness of hypoglycemia, increased frequency of blood glucose monitoring is recommended [see Warnings and Precautions (5.1)].

Administration

Instruct patients to take PRANDIN within 30 minutes before meals. Instruct patients to skip their dose of PRANDIN when a meal is skipped. [see Dosage and Administration (2)].

Drug Interactions

Discuss potential drug interactions with patients and inform them of potential drug-drug interactions with PRANDIN. [see Drug Interactions (7)].

PRANDIN® is a registered trademark of Novo Nordisk A/S.

© 2009-2017 Novo Nordisk

Manufactured for:

Novo Nordisk A/S

DK-2880 Bagsvaerd, Denmark

For information contact:
Novo Nordisk Inc.

800 Scudders Mill Road

Plainsboro, NJ 08536

1-800-727-6500

www.novonordisk-us.com